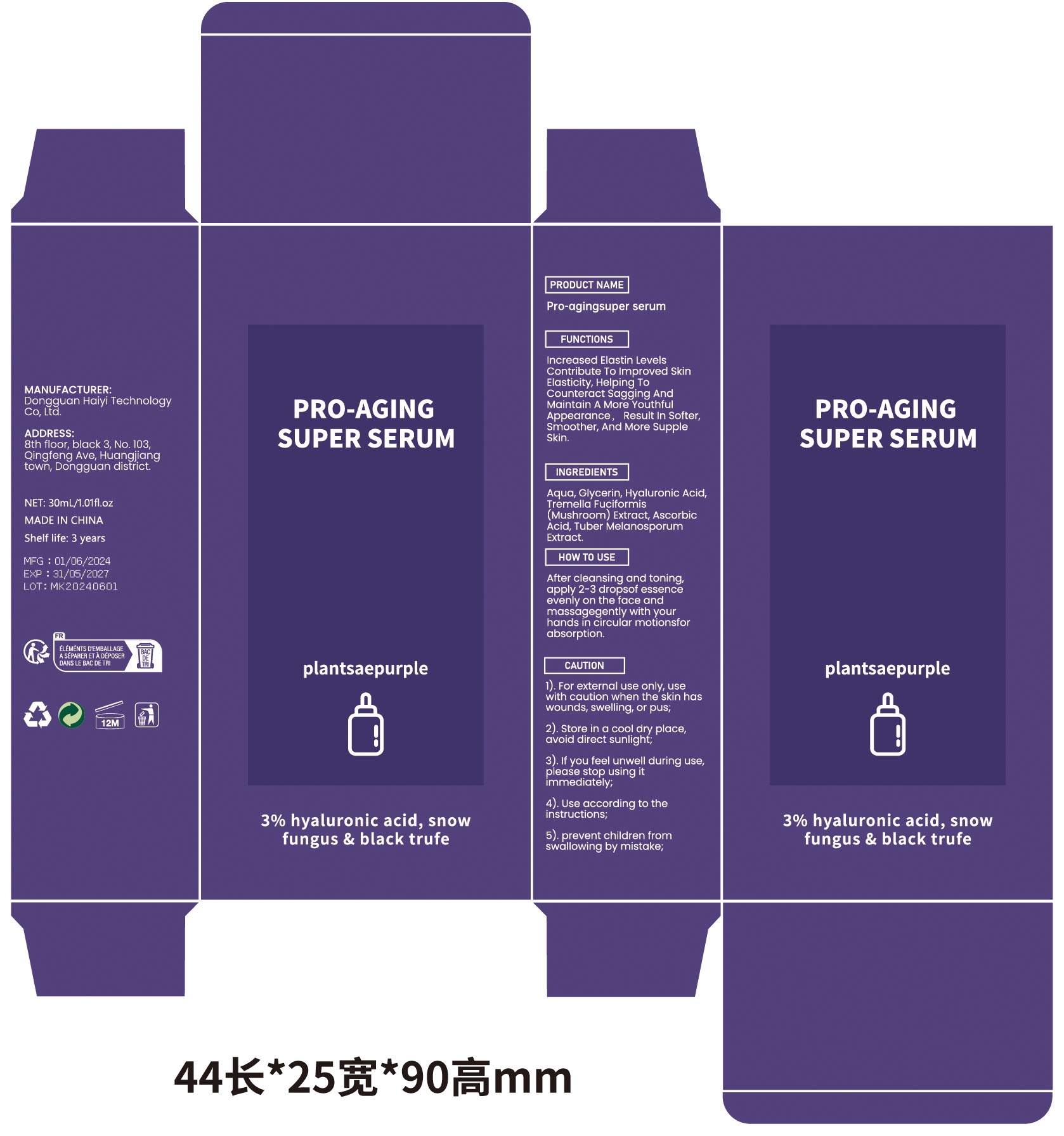 DRUG LABEL: Pro-agingsuper serum
NDC: 84732-062 | Form: LIQUID
Manufacturer: Dongguan Haiyi Technology Co.,Ltd.
Category: otc | Type: HUMAN OTC DRUG LABEL
Date: 20241023

ACTIVE INGREDIENTS: ASCORBIC ACID 1 mg/30 mL
INACTIVE INGREDIENTS: HYALURONIC ACID; WATER; GLYCERIN; TREMELLA FUCIFORMIS FRUITING BODY; BLACK TRUFFLE

Active ingredient

Tuber Melanosporum Extract

Inactive ingredient

Aqua, Glycerin, Hyaluronic Acid,Tremella Fuciformis (Mushroom) Extract, Ascorbic Acid

Purpose section

Increased Elastin Levels Contribute To lmproved Skin Elasticity, Helping To Counteract sagging And Maintain A More Youthful Appearance，Result In Softer,Smoother, And More supple Skin.

Warning

1).For external use only,usewith caution when the skin haswounds, swelling, or pus;
2). Store in a cool dry place,avoid direct sunlight;
3). lf you feel unwell during use,please stop using itimmediately,
4). Use according to theinstructions;
5). prevent children fromswallowing by mistake;

stop use

This product may cause allergic reactions in asmall number of people.
lf youexperience any discomfort,please stop using it immediately.

not use

Not suitable for use by children, pregnantor breast feeding people.

OUT OF CHILDREN

KEEP THE PRODUCT OUT OF REACH OF CHILDREN to

HOW TO USE

After cleansing and toning,apply 2-3 dropsof essenceevenly on the face andmassagegently with yourhands in circular motionsforabsorption.

Dosage

take an appropriateamount,Use 2-3 times a week